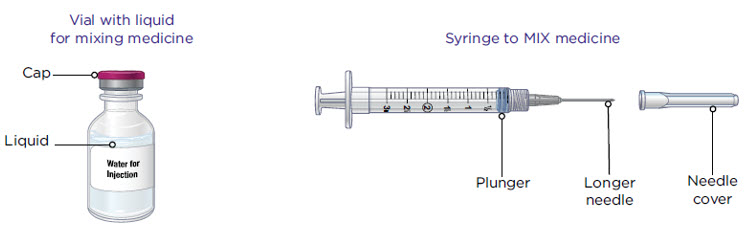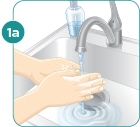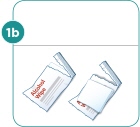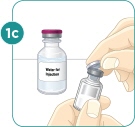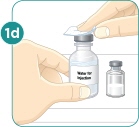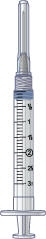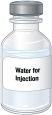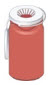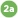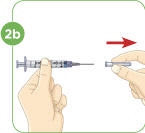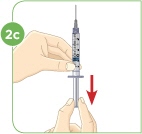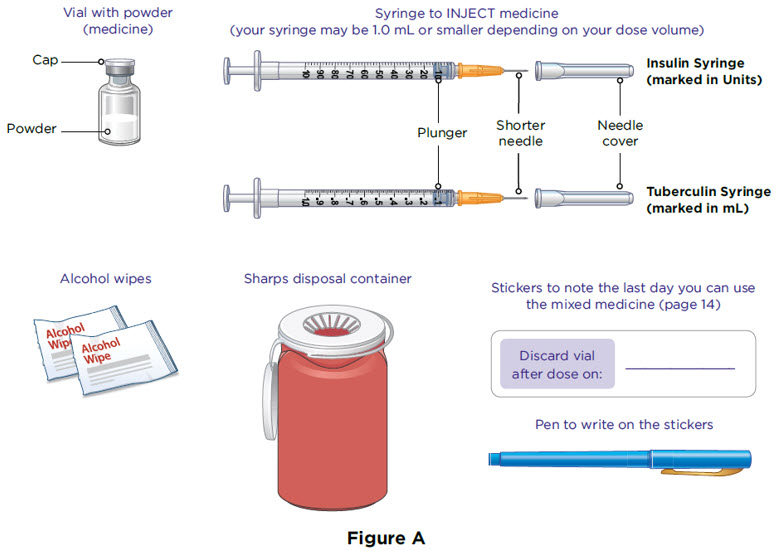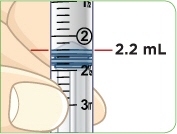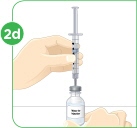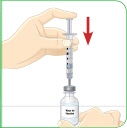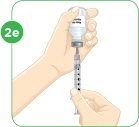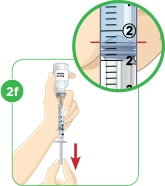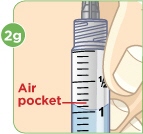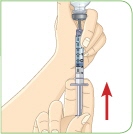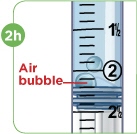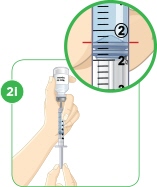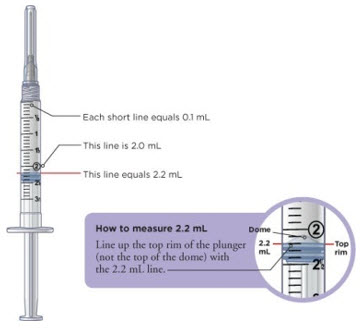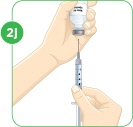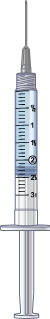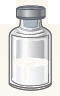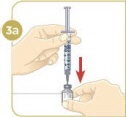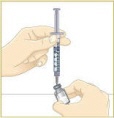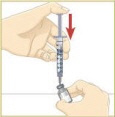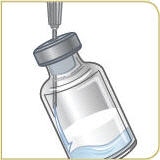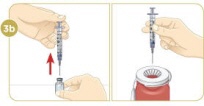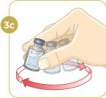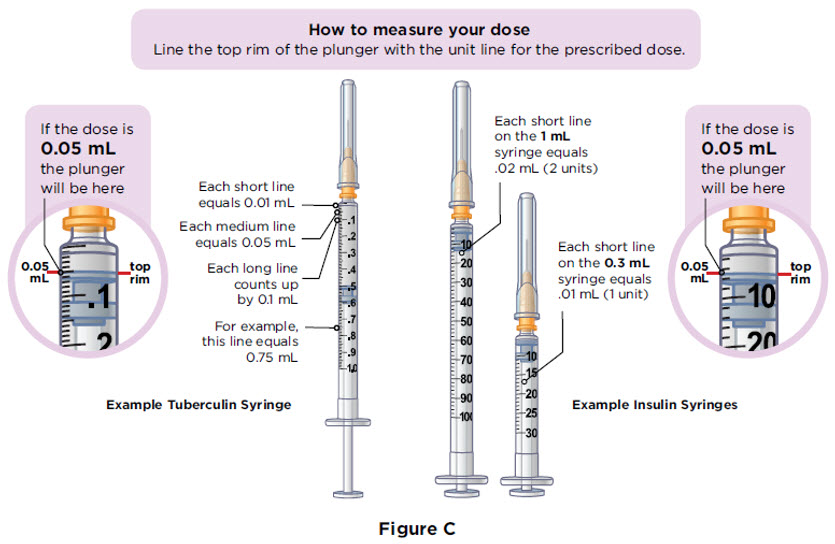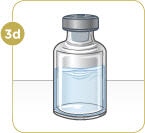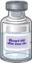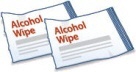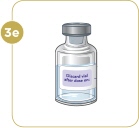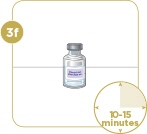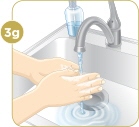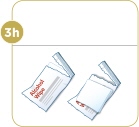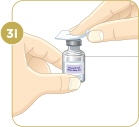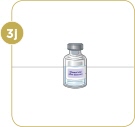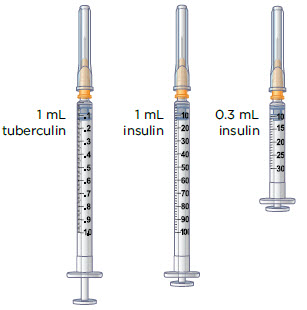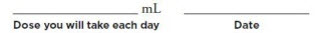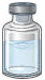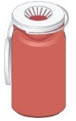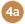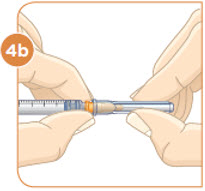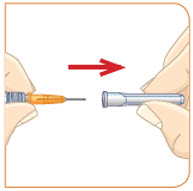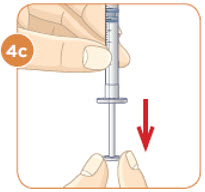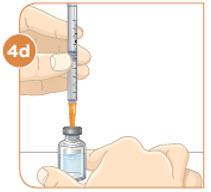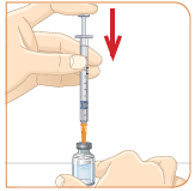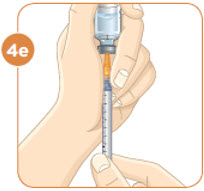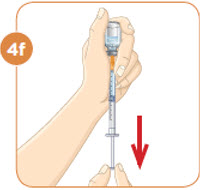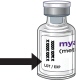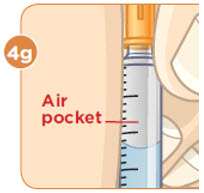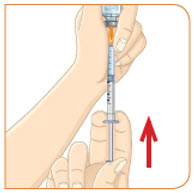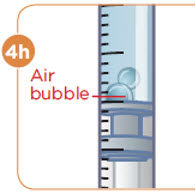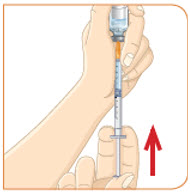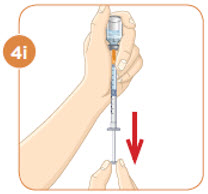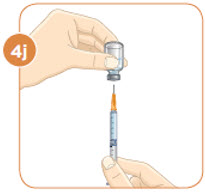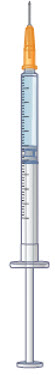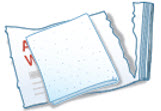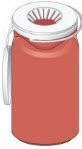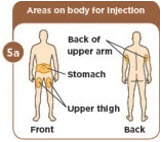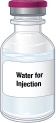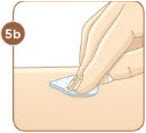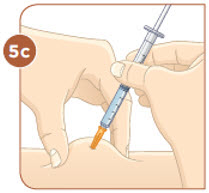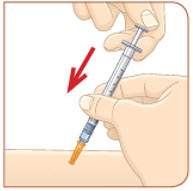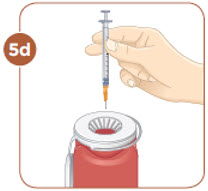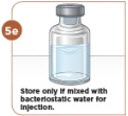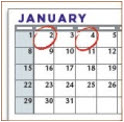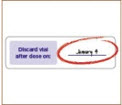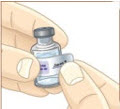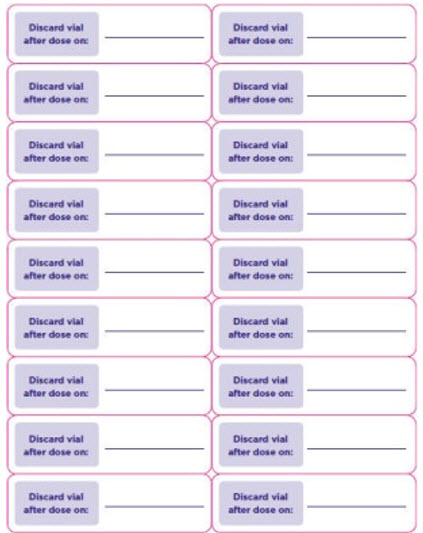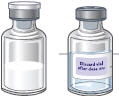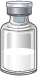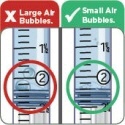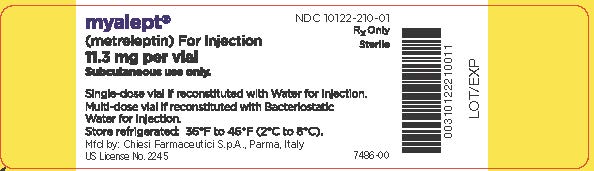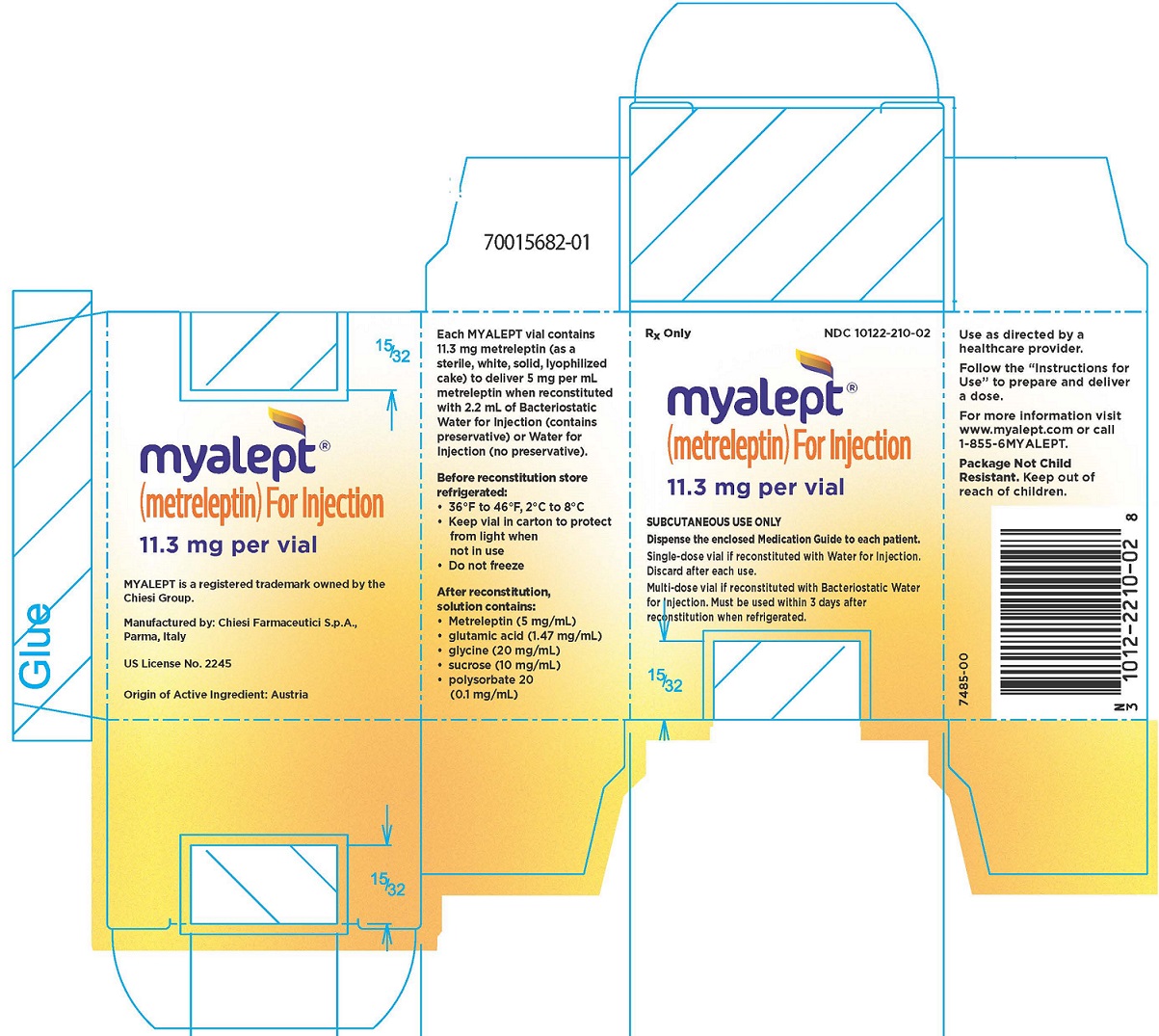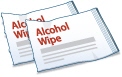 DRUG LABEL: Myalept
NDC: 10122-210 | Form: INJECTION, POWDER, LYOPHILIZED, FOR SOLUTION
Manufacturer: Chiesi USA, Inc.
Category: prescription | Type: HUMAN PRESCRIPTION DRUG LABEL
Date: 20240325

ACTIVE INGREDIENTS: Metreleptin 11.3 mg/2.2 mL
INACTIVE INGREDIENTS: Glycine; Sucrose; Polysorbate 20; Glutamic Acid

HIGHLIGHTS OF PRESCRIBING INFORMATION

These highlights do not include all the information needed to use MYALEPT safely and effectively. See full prescribing information for MYALEPT.
MYALEPT® (metreleptin) for injection, for subcutaneous use
Initial U.S. Approval: 2014

WARNING: RISK OF ANTI-METRELEPTIN ANTIBODIES WITH NEUTRALIZING ACTIVITY AND RISK OF LYMPHOMA

See full prescribing information for complete boxed warning.

Anti-metreleptin antibodies with neutralizing activity have been identified in patients treated with MYALEPT. The consequences are not well characterized but could include inhibition of endogenous leptin action and loss of MYALEPT efficacy. Worsening metabolic control and/or severe infection have been reported. Test for anti-metreleptin antibodies with neutralizing activity in patients with severe infections or loss of efficacy during MYALEPT treatment. Contact Chiesi Farmaceutici S.p.A. at 1-866-216-1526 for neutralizing antibody testing. (4.1), (5.1)

T-cell lymphoma has been reported in patients with acquired generalized lipodystrophy, both treated and not treated with MYALEPT. Carefully consider the benefits and risks of treatment with MYALEPT in patients with significant hematologic abnormalities and/or acquired generalized lipodystrophy. (5.2)

MYALEPT is available only through a restricted program called the MYALEPT REMS PROGRAM. (5.3)

1 INDICATIONS AND USAGE

MYALEPT is a leptin analog indicated as an adjunct to diet as replacement therapy to treat the complications of leptin deficiency in patients with congenital or acquired generalized lipodystrophy. (1)

Limitations of Use

- The safety and effectiveness of MYALEPT for the treatment of complications of partial lipodystrophy have not been established. (1)
- The safety and effectiveness of MYALEPT for the treatment of liver disease, including nonalcoholic steatohepatitis (NASH), have not been established. (1)
- MYALEPT is not indicated for use in patients with HIV-related lipodystrophy. (1)
- MYALEPT is not indicated for use in patients with metabolic disease, without concurrent evidence of generalized lipodystrophy. (1)

2 DOSAGE AND ADMINISTRATION

Administer as a subcutaneous injection once daily after the lyophilized cake is reconstituted with Bacteriostatic Water for Injection (BWFI) or preservative-free sterile Water for Injection (WFI). (2.1)

The recommended daily dosages are:

- Body weight 40 kg or less: starting dose 0.06 mg/kg/day, increase or decrease by 0.02 mg/kg to a maximum daily dose of 0.13 mg/kg. (2.1)
- Males greater than 40 kg body weight: starting dose 2.5 mg/day, increase or decrease by 1.25 mg to 2.5 mg/day to a maximum dose of 10 mg/day. (2.1)
- Females greater than 40 kg body weight: starting dose 5 mg/day, increase or decrease by 1.25 mg to 2.5 mg/day to a maximum dose of 10 mg/day. (2.1)

3 DOSAGE FORMS AND STRENGTHS

MYALEPT is supplied as a sterile, white, solid, lyophilized cake of 11.3 mg metreleptin per vial to deliver 5 mg per mL when reconstituted in 2.2 mL of BWFI or WFI. (3)

4 CONTRAINDICATIONS

- General obesity not associated with congenital leptin deficiency. (4.1)
- Hypersensitivity to metreleptin. (4.2)

5 WARNINGS AND PRECAUTIONS

- Anti-metreleptin antibodies with neutralizing activity: Could inhibit endogenous leptin action and/or result in loss of MYALEPT efficacy. Test for neutralizing antibodies in patients with severe infections or loss of efficacy during MYALEPT treatment. (5.1)
- T-cell lymphoma: Carefully consider benefits and risks of treatment with MYALEPT in patients with significant hematologic abnormalities and/or acquired generalized lipodystrophy. (5.2)
- Hypoglycemia: A dose adjustment, including possible large reductions, of insulin or insulin secretagogue may be necessary. Closely monitor blood glucose in patients on concomitant insulin or insulin secretagogue therapy. (5.4)
- Autoimmunity: Autoimmune disorder progression has been observed in patients treated with MYALEPT. Carefully consider benefits and risks of MYALEPT treatment in patients with autoimmune disease. (5.5)
- Hypersensitivity: Hypersensitivity reactions (e.g., anaphylaxis, urticaria or generalized rash) have been reported. Patient should promptly seek medical advice regarding suspected reactions. (5.6)
- Benzyl Alcohol Toxicity: Preservative-free sterile WFI recommended for neonates and infants. (5.7)

6 ADVERSE REACTIONS

Most common in clinical trials (≥10%): headache, hypoglycemia, decreased weight, abdominal pain. (5.4, 6.1)

To report SUSPECTED ADVERSE REACTIONS, contact Chiesi Farmaceutici S.p.A. at 1-888-661-9260 or FDA at 1-800-FDA-1088 or www.fda.gov/medwatch.

FULL PRESCRIBING INFORMATION

WARNING: RISK OF ANTI-METRELEPTIN ANTIBODIES WITH NEUTRALIZING ACTIVITY AND RISK OF LYMPHOMA

Anti-metreleptin antibodies with neutralizing activity have been identified in patients treated with MYALEPT. The consequences of these neutralizing antibodies are not well characterized but could include inhibition of endogenous leptin action and/or loss of MYALEPT efficacy. Severe infection and/or worsening metabolic control have been reported. Test for anti-metreleptin antibodies with neutralizing activity in patients who develop severe infections or show signs suspicious for loss of MYALEPT efficacy during treatment. Contact Chiesi Farmaceutici S.p.A. at 1-866-216-1526 for neutralizing antibody testing of clinical samples [see Contraindications (4.1) and Warnings and Precautions (5.1)].

T-cell lymphoma has been reported in patients with acquired generalized lipodystrophy, both treated and not treated with MYALEPT. Carefully consider the benefits and risks of treatment with MYALEPT in patients with significant hematologic abnormalities and/or acquired generalized lipodystrophy [see Warnings and Precautions (5.2)].

Because of these risks associated with the development of anti-metreleptin antibodies that neutralize endogenous leptin and/or MYALEPT and the risk for lymphoma, MYALEPT is available only through a restricted program under a Risk Evaluation and Mitigation Strategy (REMS) called the MYALEPT REMS PROGRAM [see Warnings and Precautions (5.3)].

1 INDICATIONS AND USAGE

1.1 Patients with Generalized Lipodystrophy

MYALEPT (metreleptin) for injection is indicated as an adjunct to diet as replacement therapy to treat the complications of leptin deficiency in patients with congenital or acquired generalized lipodystrophy.

Limitations of Use

- The safety and effectiveness of MYALEPT for the treatment of complications of partial lipodystrophy have not been established.
- The safety and effectiveness of MYALEPT for the treatment of liver disease, including nonalcoholic steatohepatitis (NASH), have not been established.
- MYALEPT is not indicated for use in patients with HIV-related lipodystrophy.
- MYALEPT is not indicated for use in patients with metabolic disease, including diabetes mellitus and hypertriglyceridemia, without concurrent evidence of congenital or acquired generalized lipodystrophy.

2 DOSAGE AND ADMINISTRATION

2.1 Recommended Dosing

See Table 1 for the recommended daily dose and maximum recommended daily dose in adults and pediatric patients.

Based on clinical response (e.g., inadequate metabolic control) or other considerations (e.g., tolerability issues, excessive weight loss [especially in pediatric patients]), MYALEPT dosage may be decreased or increased to the maximum dosage listed in Table 1.

Table 1: MYALEPT Recommended Dosage
Baseline weight | Starting daily dose (injection volume) | Dose adjustments (injection volume) | Maximum daily dose (injection volume)
Less than or equal to 40 kg (males and females) | 0.06 mg/kg (0.012 mL/kg) | 0.02 mg/kg (0.004 mL/kg) | 0.13 mg/kg (0.026 mL/kg)
Males greater than 40 kg | 2.5 mg (0.5 mL) | 1.25 mg (0.25 mL) to 2.5 mg (0.5 mL) | 10 mg (2 mL)
Females greater than 40 kg | 5 mg (1 mL) | 1.25 mg (0.25 mL) to 2.5 mg (0.5 mL) | 10 mg (2 mL)

In pediatric patients, small volumes for administration can result in medication errors when measured incorrectly [see Dosage and Administration (2.3), Adverse Reactions (6.3)]. Table 2 provides example doses and volumes by weight. For patients using insulin syringes, the volume conversion is 100 Units/mL.

Table 2: Example Dosing Chart for Patients Less than or Equal to 40 kg
Weight | Starting Dose | Dose Adjustment | Maximum Dose
5 kg | 0.30 mg (0.06 mL or 6 Units) | 0.10 mg (0.02 mL or 2 Units) | 0.65 mg (0.13 mL or 13 Units)
10 kg | 0.60 mg (0.12 mL or 12 Units) | 0.20 mg (0.04 mL or 4 Units) | 1.3 mg (0.26 mL or 26 Units)
15 kg | 0.90 mg (0.18 mL or 18 Units) | 0.30 mg (0.06 mL or 6 Units) | 1.95 mg (0.39 mL or 39 Units)
20 kg | 1.2 mg (0.24 mL or 24 Units) | 0.40 mg (0.08 mL or 8 Units) | 2.6 mg (0.52 mL or 52 Units)
25 kg | 1.5 mg (0.3 mL or 30 Units) | 0.50 mg (0.1 mL or 10 Units) | 3.25 mg (0.65 mL or 65 Units)
30 kg | 1.8 mg (0.36 mL or 36 Units) | 0.60 mg (0.12 mL or 12 Units) | 3.9 mg (0.78 mL or 78 Units)
35 kg | 2.1 mg (0.42 mL or 42 Units) | 0.70 mg (0.14 mL or 14 Units) | 4.55 mg (0.91 mL or 91 Units)
40 kg | 2.4 mg (0.48 mL or 48 Units) | 0.80 mg (0.16 mL or 16 Units) | 5.2 mg (1.03 mL or 103 Units)

MYALEPT should be administered once daily at the same time every day. MYALEPT can be administered any time of day without regard to the timing of meals.

Instruct patients that if a dose is missed, administer the dose as soon as noticed, and resume the normal dosing schedule the next day.

2.2 MYALEPT Preparation and Storage

Healthcare practitioners should provide proper training to patients and caregivers regarding how to prepare and administer the correct dose of MYALEPT prior to self-use. The patients and caregivers should prepare and administer the first dose of MYALEPT under the supervision of a qualified healthcare professional.

Instruct patients to store the vials of lyophilized powder in their carton in the refrigerator as soon as received [see How Supplied/Storage and Handling (16.2)].

MYALEPT can be reconstituted aseptically with 2.2 mL of sterile Bacteriostatic Water for Injection (BWFI), USP (0.9% benzyl alcohol), or with 2.2 mL of sterile Water for Injection (WFI).

When reconstituted in BWFI, MYALEPT solution can be used within 3 days when stored in the refrigerator between 36°F and 46°F (2°C and 8°C) and protected from light [see How Supplied/Storage and Handling (16.2)]. Discard unused reconstituted solution after 3 days. Attach the supplied sticker to the vial and enter the discard date.

For use in neonates and infants, reconstitute with preservative-free sterile WFI [see Warnings and Precautions (5.7) and Use in Specific Populations (8.4)]. When reconstituted in sterile WFI, MYALEPT should be administered immediately. Unused reconstituted solution cannot be saved for later use and should be discarded.

Reconstitution of the Lyophilized Powder

Instruct patients to follow the directions below for reconstitution of the lyophilized powder:

1. Remove the vial containing the MYALEPT lyophilized powder from the refrigerator and allow the vial to warm to room temperature prior to use.
2. Visually inspect the vial containing MYALEPT. The cake of lyophilized powder should be intact and white in color.
3. Using a 3-mL syringe with a 22-gauge or smaller diameter needle withdraw 2.2 mL of sterile Bacteriostatic Water for Injection (BWFI) or preservative-free sterile Water for Injection (WFI). Do not reconstitute MYALEPT with other diluents.
4. Inject the BWFI or WFI into the vial containing the lyophilized powder of MYALEPT, slowly injecting down the side of the vial. It is normal for some bubbles to form.
5. Remove the needle and syringe from the vial and gently swirl the contents to reconstitute. Do not shake or vigorously agitate. When properly mixed, the MYALEPT reconstituted solution should be clear and free of clumps or dry powder, bubbles or foam. Do not use the solution if discolored or cloudy, or if particulate matter remains.
6. Regarding the compatibility of MYALEPT reconstituted solution with other solutions:
  - Do not mix with, or transfer into, the contents of another vial of MYALEPT.
  - Do not add other medications, including insulin. Use a separate syringe for insulin injections.

See the MYALEPT Instructions for Use for complete administration instructions. The instructions can also be found at www.myalept.com.

2.3 Administration Instructions

Healthcare practitioners should instruct patients and caregivers on the proper subcutaneous injection technique with care to avoid intramuscular injection in patients with minimal subcutaneous adipose tissue. Never administer MYALEPT intravenously or intramuscularly.

Instruct patients to follow the recommended injection technique:

1. Using a 1-mL or smaller syringe with a needle appropriate for subcutaneous injection, withdraw the prescribed dose of MYALEPT reconstituted solution.
2. Remove any large air pockets or large bubbles from the filled syringe prior to administration. Some small bubbles may remain in the syringe.
3. Administer MYALEPT into the subcutaneous tissue of the abdomen, thigh or upper arm. Advise patients to use a different injection site each day when injecting in the same region. After choosing an injection site, pinch the skin and at a 45-degree angle, inject the MYALEPT reconstituted solution subcutaneously. Avoid intramuscular injection, especially in patients with minimal subcutaneous adipose tissue.
4. Doses exceeding 1 mL can be administered as two injections (the total daily dose divided equally) to minimize potential injection-site discomfort due to injection volume. When dividing doses due to volume, doses can be administered one after the other.
5. In pediatric patients, small volumes for administration can result in medication errors when measured incorrectly. Smaller syringe sizes may be more appropriate for pediatric patients weighing less than or equal to 25 kg. Ensure the proper size syringe is selected. Table 2 provides example doses and volumes by weight [see Dosage and Administration (2.1), Adverse Reactions (6.3)].

Do not mix MYALEPT with insulin. Use a separate syringe for each medication. If MYALEPT and insulin are administered at the same time of day, they may be injected in the same body area using two different injection sites.

See the MYALEPT Instructions for Use for complete administration instructions. The instructions can also be found at www.myalept.com.

2.4 Dosage Adjustments of Medications Known to Cause Hypoglycemia

Dosage adjustments, including possible large reductions, of insulin or insulin secretagogue (e.g., sulfonylurea) may be necessary in some patients to minimize the risk of hypoglycemia [see Warnings and Precautions (5.4) and Adverse Reactions (6.1)]. Closely monitor blood glucose in patients on concomitant insulin therapy, especially those on high doses, or insulin secretagogue (e.g., sulfonylurea) when treating with MYALEPT.

2.5 Discontinuation in Patients at Risk for Pancreatitis

When discontinuing MYALEPT therapy in patients with risk factors for pancreatitis (e.g., history of pancreatitis, severe hypertriglyceridemia), tapering of the dose over a one-week period is recommended. During tapering, monitor triglyceride levels and consider initiating or adjusting the dose of lipid-lowering medications as needed. Signs and/or symptoms consistent with pancreatitis should prompt an appropriate clinical evaluation.

3 DOSAGE FORMS AND STRENGTHS

For Injection: 11.3 mg of metreleptin supplied in a vial as a sterile, white, solid, lyophilized cake (delivers 5 mg per mL of metreleptin when reconstituted with 2.2 mL of BWFI or WFI).

4 CONTRAINDICATIONS

4.1 General Obesity

MYALEPT is contraindicated in patients with general obesity not associated with congenital leptin deficiency. MYALEPT has not been shown to be effective in treating general obesity, and the development of anti-metreleptin antibodies with neutralizing activity has been reported in obese patients treated with MYALEPT [see Warnings and Precautions (5.1)].

4.2 Hypersensitivity

MYALEPT is contraindicated in patients with prior severe hypersensitivity reactions to metreleptin or to any of the product components. Known hypersensitivity reactions have included anaphylaxis, urticaria and generalized rash [see Warnings and Precautions (5.6)].

5 WARNINGS AND PRECAUTIONS

5.1 Risk for Development of Antibodies that Neutralize Endogenous Leptin and/or MYALEPT

Anti-metreleptin antibodies with in vitro neutralizing activity to leptin associated with adverse events consistent with loss of endogenous leptin activity and/or loss of efficacy have been identified in two patients with generalized lipodystrophy treated with MYALEPT (severe infections, increases in HbA1c and triglycerides), and in three patients without lipodystrophy who received MYALEPT in clinical studies (excessive weight gain, development of glucose intolerance or diabetes mellitus). The clinical implications associated with development of anti-metreleptin antibodies with neutralizing activity are not well characterized at this time due to the small number of reports. Test for anti-metreleptin antibodies with neutralizing activity in patients who develop severe infections or show signs suspicious for loss of MYALEPT efficacy during treatment. Contact Chiesi Farmaceutici S.p.A. at 1-866-216-1526 for neutralizing antibody testing of clinical samples [see Adverse Reactions (6.2)].

5.2 Lymphoma

Three cases of T-cell lymphoma have been reported in the MYALEPT lipodystrophy program; all three patients had acquired generalized lipodystrophy. Two of these patients were diagnosed with peripheral T-cell lymphoma while receiving MYALEPT. Both had immunodeficiency and significant hematologic abnormalities including severe bone marrow abnormalities before the start of MYALEPT treatment. A separate case of anaplastic large cell lymphoma was reported in a patient receiving MYALEPT who did not have hematological abnormalities before treatment.

Lymphoproliferative disorders, including lymphomas, have been reported in patients with acquired generalized lipodystrophy not treated with MYALEPT. A causal relationship between MYALEPT treatment and the development and/or progression of lymphoma has not been established. Acquired lipodystrophies are associated with autoimmune disorders, and autoimmune disorders are associated with an increased risk of malignancies including lymphomas.

The benefits and risks of MYALEPT treatment should be carefully considered in patients with acquired generalized lipodystrophy and/or those with significant hematologic abnormalities (including leukopenia, neutropenia, bone marrow abnormalities, lymphoma, and/or lymphadenopathy).

5.3 MYALEPT REMS Program

MYALEPT is available only through a restricted distribution program under a REMS, called the MYALEPT REMS Program, because of the risks associated with the development of anti-metreleptin antibodies that neutralize endogenous leptin and/or MYALEPT and the risk for lymphoma [see Warnings and Precautions (5.1, 5.2)].

Notable requirements of the MYALEPT REMS Program include the following:

- Prescribers must be certified with the program by enrolling and completing training.
- Pharmacies must be certified with the program and only dispense MYALEPT after receipt of the MYALEPT REMS Prescription Authorization Form for each new prescription.

Further information is available at www.myaleptrems.com or 1-855-669-2537.

5.4 Hypoglycemia with Concomitant Use with Insulin and Insulin Secretagogues

Dosage adjustments, including possible large reductions, of insulin or insulin secretagogue (e.g., sulfonylurea) may be necessary in some patients to minimize the risk of hypoglycemia [see Dosage and Administration (2.4) and Adverse Reactions (6.1)]. Closely monitor blood glucose in patients on concomitant insulin therapy, especially those on high doses, or insulin secretagogue (e.g., sulfonylurea), when treating with MYALEPT.

5.5 Autoimmunity

Leptin plays a role in immune system homeostasis. Acquired lipodystrophies are associated with autoimmune disorders including autoimmune hepatitis and membranoproliferative glomerulonephritis. Cases of progression of autoimmune hepatitis and membranoproliferative glomerulonephritis (associated with massive proteinuria and renal failure) were observed in some patients with acquired generalized lipodystrophy treated with MYALEPT. A causal relationship between MYALEPT treatment and the development and/or progression of autoimmune disease has not been established. The potential benefits and risks of MYALEPT treatment should be carefully considered in patients with autoimmune disease.

5.6 Hypersensitivity

There have been reports of generalized hypersensitivity (e.g., anaphylaxis, urticaria or generalized rash) in patients taking MYALEPT. If a hypersensitivity reaction occurs, instruct the patient to promptly seek medical advice regarding discontinuation of MYALEPT.

5.7 Benzyl Alcohol Toxicity

MYALEPT contains benzyl alcohol when reconstituted with BWFI. MYALEPT contains no preservative when reconstituted with sterile Water for Injection (WFI). Preservative-free WFI is recommended for use in neonates and infants. The preservative benzyl alcohol has been associated with serious adverse events and death in pediatric patients, particularly in neonates and premature infants [see Use in Specific Populations (8.4)].

6 ADVERSE REACTIONS

6.1 Clinical Trials Experience

Because clinical trials are conducted under widely varying conditions, adverse reaction rates observed in the clinical trials of a drug cannot be directly compared to rates in the clinical trials of another drug and may not reflect the rates observed in practice.

Open-Label, Single-Arm Study

The safety of MYALEPT was evaluated in 48 patients with generalized lipodystrophy in a single-arm, open-label study [see Clinical Studies (14.1)]. The median duration of exposure in this trial was 2.7 years with a range of 3.6 months to 10.9 years. The most frequent adverse reactions are summarized in Table 3.

Table 3: Adverse Reactions of 5% or Greater Incidence in Patients with Generalized Lipodystrophy Receiving MYALEPT in an Open-Label, Single-Arm Study
 | All Subjects N=48 (%)
Headache | 6 (13)
Hypoglycemia^1 | 6 (13)
Decreased weight | 6 (13)
Abdominal pain | 5 (10)
Arthralgia | 4 (8)
Dizziness | 4 (8)
Ear infection | 4 (8)
Fatigue | 4 (8)
Nausea | 4 (8)
Ovarian cyst | 4 (8)
Upper respiratory tract infection | 4 (8)
Anemia | 3 (6)
Back pain | 3 (6)
Diarrhea | 3 (6)
Paresthesia | 3 (6)
Proteinuria | 3 (6)
Pyrexia | 3 (6)
^1. Hypoglycemic events were assessed as mild, moderate, severe, or life threatening based on the protocol specified definitions: Mild: Documentation of low plasma glucose values with no symptoms; Moderate: Presence of clinical symptoms requiring ingestion of glucose, self-alleviated; Severe: Presence of neuroglycopenic symptoms requiring assistance from others for alleviation; Life threatening: Loss of consciousness and/or requiring intervention by administration of intravenous glucose or intramuscular glucagon.

In patients with generalized lipodystrophy receiving MYALEPT in this study, less common adverse reactions included injection-site erythema and urticaria (N=2 [4%]).

Six patients (13%) had 7 adverse reactions of hypoglycemia, 6 of which occurred in the setting of concomitant insulin use, with or without oral antihyperglycemic agents.

Two patients (4%) had events of pancreatitis, both of whom had a medical history of pancreatitis.

6.2 Immunogenicity

As with all therapeutic proteins, there is potential for immunogenicity. Anti-metreleptin antibodies were detected in 84% (36/43) of generalized lipodystrophy patients studied in the MYALEPT trials. Total anti-metreleptin antibody titers ranged between 1:5 and 1:1,953,125. The incompleteness of the current immunogenicity database precludes understanding of the magnitude and persistence of the observed anti-drug antibody responses. Anti-metreleptin antibodies with neutralizing activity associated with adverse events consistent with loss of endogenous leptin activity and/or loss of MYALEPT efficacy were observed in 6% (2/33) of the patients with generalized lipodystrophy tested. Adverse events reported in these two patients included severe infections and worsening of metabolic control (increases in HbA1c and/or triglycerides). Test for anti-metreleptin antibodies with neutralizing activity in patients who develop severe infections or show signs suspicious for loss of MYALEPT efficacy during treatment. Contact Chiesi Farmaceutici S.p.A. at 1-866-216-1526 for testing of clinical samples.

The detection of antibody formation is highly dependent on the sensitivity and specificity of the assay. The immunogenicity assays utilized in clinical trials lacked sensitivity, resulting in potential underestimation of the number of samples positive for anti-metreleptin antibodies with neutralizing activity. Additionally, the observed incidence of antibody (including neutralizing antibody) positivity in an assay may be influenced by several factors including assay methodology, sample handling, timing of sample collection, concomitant medications, and underlying disease. For these reasons, comparison of the incidence of antibodies to metreleptin with the incidence of antibodies to other products may be misleading.

6.3 Postmarketing Experience

The following adverse reactions have been identified during post-approval use of MYALEPT. Because these reactions are reported voluntarily from a population of uncertain size, it is not always possible to reliably estimate their frequency or establish a causal relationship to drug exposure.

- Incorrect dose administered, accidental overdose [see Dosage and Administration (2.1, 2.3)]
- Injection site reaction, including inflammation and hyperpigmentation

7 DRUG INTERACTIONS

No formal drug interaction studies were performed.

Leptin is a cytokine and may have the potential to alter the formation of cytochrome P450 (CYP450) enzymes. This should be taken into account when prescribing concomitant drugs metabolized by CYP450 (e.g., oral contraceptives and drugs with a narrow therapeutic index). The effect of metreleptin on CYP450 enzymes may be clinically relevant for CYP450 substrates with narrow therapeutic index, where the dose is individually adjusted. Upon initiation or discontinuation of MYALEPT, in patients being treated with these types of agents, therapeutic monitoring of effect (e.g., warfarin) or drug concentration (e.g., cyclosporine or theophylline) should be performed and the individual dose of the agent adjusted as needed.

8 USE IN SPECIFIC POPULATIONS

8.1 Pregnancy

Pregnancy Exposure Registry

There is a program that monitors outcomes in women exposed to MYALEPT during pregnancy. Women who become pregnant during MYALEPT treatment are encouraged to enroll. Patients or their physicians should call 1-855-669-2537 to enroll.

Risk Summary

Available pharmacovigilance reports with the use of MYALEPT in pregnant women are insufficient to evaluate for any drug-associated risk for major birth defects, miscarriage, or adverse maternal or fetal outcomes. These reports describe similar adverse pregnancy outcomes as those documented in women with lipodystrophy (see Clinical Considerations). In an animal reproduction study, no adverse developmental effects were observed with subcutaneous administration of metreleptin to pregnant mice during organogenesis at doses 7- and 15-fold the maximum recommended clinical dose, based on body surface area of a 20- and 60-kg patient, respectively. In a pre- and postnatal development study in mice, subcutaneous administration of metreleptin caused prolonged gestation and dystocia resulting in maternal death during parturition and lower survival of offspring in the immediate postnatal period at doses starting approximately at the maximum recommended clinical dose (see Data).

MYALEPT contains benzyl alcohol when reconstituted with BWFI. MYALEPT contains no preservative when reconstituted with WFI. Because benzyl alcohol is rapidly metabolized by a pregnant woman, benzyl alcohol exposure in the fetus is unlikely. However, adverse reactions have occurred in premature neonates and low birth weight infants who received intravenously administered benzyl alcohol-containing drugs [see Warnings and Precautions (5.7) and Use in Specific Populations (8.4)]. Therefore, if therapy with MYALEPT is needed during pregnancy, consider using preservative-free WFI when reconstituting [see Dosage and Administration (2.2)].

The estimated background risk of major birth defects and miscarriage for the indicated population is unknown. In the U.S. general population, the estimated background risks of major birth defects and miscarriage in clinically recognized pregnancies is 2-4% and 15-20%, respectively.

Clinical Considerations

Disease-Associated Maternal and Fetal Risk

Lipodystrophy in pregnancy can result in an increased rate of gestational diabetes, macrosomia, eclampsia, intrauterine growth retardation, intrauterine death, and miscarriage.

Labor and Delivery

The effects of MYALEPT on labor and delivery in pregnant women are unknown. In a published in vitro study of human myometrial tissue exposed to a recombinant leptin, human uterine contractility was inhibited. In animal studies with metreleptin, prolonged gestation and dystocia were observed (see Data).

Data

Animal Data

Metreleptin administered to pregnant mice during the period of organogenesis was not teratogenic at doses ranging between 7- and 15-fold the maximum recommended clinical dose, based on body surface area of a 20- and 60-kg patient, respectively.

In a pre- and postnatal development study in mice, metreleptin administered at doses of 3, 10, and 30 mg/kg (approximately 1-, 5-, and 15-fold the clinical dose for a 60-kg subject, based on body surface area) from gestation day 6 to lactation day 21 caused prolonged gestation and dystocia at all doses, starting at approximately the maximum recommended clinical dose. Prolonged gestation resulted in the death of some females during parturition and lower survival of offspring within the immediate postnatal period. Consistent with metreleptin pharmacology, decreased maternal body weight was observed from gestation throughout lactation at all doses and resulted in reduced weight of offspring at birth, which persisted into adulthood. However, no developmental abnormalities were observed and reproductive performance of the first or second generations was not affected at any dose.

Placental transfer of metreleptin into the fetus was low (approximately 1%) following subcutaneous dosing.

8.2 Lactation

There are no available data on the presence of metreleptin in human milk; however, endogenous leptin is present in human milk. There are no available data on the effects of metreleptin on the breastfed infant or the effects on milk production. The developmental and health benefits of breastfeeding should be considered along with the mother's clinical need for MYALEPT and any potential adverse effects on the breastfed child from MYALEPT or from the underlying maternal condition.

8.4 Pediatric Use

The MYALEPT study included a total of 35 pediatric patients (73%) with an age range from 1 to 17 years [see Clinical Studies (14.1)]. No clinically meaningful differences were observed in the efficacy and safety of MYALEPT between pediatric and adult patients.

MYALEPT contains benzyl alcohol when reconstituted with BWFI. MYALEPT contains no preservative when reconstituted with WFI. Preservative-free WFI is recommended for use in neonates and infants. The preservative benzyl alcohol has been associated with serious adverse events and death, particularly in pediatric patients. The "gasping syndrome" (characterized by central nervous system depression, metabolic acidosis, gasping respirations, and high levels of benzyl alcohol and its metabolites found in the blood and urine) has been associated with benzyl alcohol dosages >99 mg/kg/day in neonates and low-birth weight infants. Additional symptoms may include gradual neurological deterioration, seizures, intracranial hemorrhage, hematologic abnormalities, skin breakdown, hepatic and renal failure, hypotension, bradycardia, and cardiovascular collapse.

Although normal therapeutic doses of this product deliver amounts of benzyl alcohol that are substantially lower than those reported in association with the "gasping syndrome," the minimum amount of benzyl alcohol at which toxicity may occur is not known. Premature and low-birth-weight infants, as well as patients receiving high dosages, may be more likely to develop toxicity. Practitioners administering this and other medications containing benzyl alcohol should consider the combined daily metabolic load of benzyl alcohol from all sources. When reconstituted with 2.2 mL of BWFI, MYALEPT contains 1.76 mg of benzyl alcohol per mg of metreleptin or 9 mg of benzyl alcohol per mL of reconstituted product.

8.5 Geriatric Use

Clinical trials of MYALEPT did not include sufficient numbers of subjects aged 65 and over (n=1) to determine whether they respond differently from younger subjects. In general, dose selection for an elderly patient should be cautious, usually starting at the low end of the dosing range, reflecting the greater frequency of decreased hepatic, renal, or cardiac function, and of concomitant disease or other drug therapy.

10 OVERDOSAGE

In one post-marketing case, a dose miscalculation resulted in an infant being exposed to a 10-fold overdose of metreleptin for 8 months. In this case, prolonged overdose was associated with severe anorexia causing vitamin and zinc deficiencies, iron deficiency anemia, protein calorie malnutrition, and poor weight gain, which resolved following supportive treatment and dose adjustment.

In the event of an overdose, patients should be monitored and appropriate supportive treatment be initiated as dictated by the patient's clinical status.

11 DESCRIPTION

MYALEPT (metreleptin) for injection is a recombinant human leptin analog for injection that binds to and activates the leptin receptor. Metreleptin (recombinant methionyl-human leptin) is produced in E. coli and differs from native human leptin by the addition of a methionine residue at its amino terminus. Metreleptin is a 147-amino acid, nonglycosylated, polypeptide with one disulfide bond between Cys-97 and Cys-147 and a molecular weight of approximately 16.15 kDa.

MYALEPT is supplied as a sterile, white, solid, lyophilized cake containing 11.3 mg that is reconstituted with 2.2 mL of BWFI or WFI to a final formulation of 5 mg/mL metreleptin for subcutaneous injection. Inactive ingredients are: glutamic acid (1.47 mg/mL), glycine (20 mg/mL), polysorbate 20 (0.1 mg/mL), and sucrose (10 mg/mL), pH 4.25.

12 CLINICAL PHARMACOLOGY

12.1 Mechanism of Action

Adipocytes store lipids to meet the fuel requirements of non-adipose tissues during fasting. In patients with generalized lipodystrophy, the deficiency of adipose tissue leads to hypertriglyceridemia and ectopic deposition of fat in non-adipose tissues such as liver and muscle, contributing to metabolic abnormalities including insulin resistance. Native leptin is a hormone predominantly secreted by adipose tissue that informs the central nervous system of the status of energy stores in the body. In patients with generalized lipodystrophy, leptin deficiency, resulting from the loss of adipose tissue, contributes to excess caloric intake, which exacerbates the metabolic abnormalities.

MYALEPT (metreleptin) for injection exerts its function by binding to and activating the human leptin receptor (ObR), which belongs to the Class I cytokine family of receptors that signals through the JAK/STAT transduction pathway.

12.2 Pharmacodynamics

Clinical studies in patients with generalized lipodystrophy suggest that MYALEPT increases insulin sensitivity and reduces food intake. Improvements in insulin sensitivity and reductions in food intake are consistent with lower HbA1c, fasting glucose, and fasting triglyceride values that were seen in the MYALEPT clinical trial [see Clinical Studies (14)].

12.3 Pharmacokinetics

There are limited data on the pharmacokinetics of metreleptin in patients with generalized lipodystrophy, and therefore, no formal exposure-response analysis has been performed. It should be noted that the leptin assay measures both endogenous leptin as well as exogenously administered metreleptin.

Absorption

Peak serum leptin concentration (Cmax) occurred approximately 4.0 to 4.3 hours after subcutaneous administration of single doses ranging from 0.1 to 0.3 mg/kg in healthy subjects. In a supportive trial in lipodystrophy patients, the median Tmax of metreleptin was 4 hours (range: 2 to 8 hours; N=5) following single-dose administration of metreleptin.

Distribution

In studies of healthy adult subjects, following intravenous administration of metreleptin, leptin volume of distribution was approximately 4 to 5 times plasma volume; volumes (Vz) (mean ± SD) were 370 ± 184 mL/kg, 398 ± 92 mL/kg, and 463 ± 116 mL/kg for 0.3, 1.0, and 3.0 mg/kg/day doses, respectively.

Metabolism and Elimination

No formal metabolism studies have been conducted with metreleptin. Nonclinical data indicate renal clearance is the major route of metreleptin elimination, with no apparent contribution of systemic metabolism or degradation. Following single subcutaneous doses of 0.01 to 0.3 mg/mL metreleptin in healthy subjects, the half-life was 3.8 to 4.7 hours. The clearance of metreleptin is expected to be delayed in the presence of leptin antibodies [see Adverse Reactions (6.2)].

Drug Interactions

No drug interaction studies have been conducted in lipodystrophy patients [see Drug Interactions (7)].

Specific Populations

Renal Impairment

No formal pharmacokinetic studies were conducted in patients with renal impairment. Nonclinical data indicate renal clearance is the major route of metreleptin elimination, with no apparent contribution of systemic metabolism or degradation. Hence, the pharmacokinetics of metreleptin may be altered in subjects with renal impairment.

Hepatic Impairment

No formal pharmacokinetic studies were conducted in patients with hepatic impairment.

Age, Gender, Race, Body Mass Index

Specific clinical studies have not been conducted to assess the effect of age, gender, race, or body mass index on the pharmacokinetics of metreleptin in patients with generalized lipodystrophy.

13 NONCLINICAL TOXICOLOGY

13.1 Carcinogenesis, Mutagenesis, Impairment of Fertility

Two-year carcinogenicity studies in rodents have not been conducted with metreleptin. No proliferative or preneoplastic lesions were observed in mice or dogs following treatment up to six months. However, leptin is reported in the literature to promote cell proliferation in vitro and tumor progression in some mouse models of cancer.

Metreleptin was not mutagenic in the Ames bacterial mutagenicity assay or clastogenic in an in vitro chromosomal aberration assay in Chinese hamster ovary cells and human peripheral blood lymphocytes. Metreleptin was not mutagenic or clastogenic in an in vivo mouse micronucleus assay.

In a fertility study in mice, metreleptin had no adverse effects on mating, fertility, or early embryonic development at doses ranging between 7 and 15 times the maximum recommended clinical dose based on body surface area of a 20- and 60-kg patient, respectively.

14 CLINICAL STUDIES

14.1 Open-Label, Single-Arm Study

An open-label, single-arm study evaluated MYALEPT treatment in patients with congenital or acquired generalized lipodystrophy and diabetes mellitus, hypertriglyceridemia, and/or increased fasting insulin.

Baseline Disease Characteristics and Demographics

Of the 48 patients enrolled, 32 (67%) had congenital generalized lipodystrophy and 16 (33%) had acquired generalized lipodystrophy. Overall, 36 (75%) patients were female, 22 (46%) were Caucasian, 10 (21%) Hispanic, and 9 (19%) Black. The median age at baseline was 15 years (range: 1 - 68 years), with 35 (73%) patients being less than 18 years of age. The median fasting leptin concentration at baseline was 0.7 ng/mL in males (range: 0.3 - 3.3 ng/mL) and 1.0 ng/mL in females (range: 0.3 - 3.3 ng/mL).

Treatment Duration and Dosage in the Study

The median duration of MYALEPT treatment was 2.7 years (range: 3.6 months - 10.9 years). MYALEPT was administered subcutaneously either once daily or twice daily (in two equal doses). The weighted average daily dose (i.e., the average dose taking into account duration of treatment at different doses) for the 36 patients with baseline body weight greater than 40 kg was 2.6 mg for males and 4.6 mg for females during the first year of treatment, and 3.2 mg for males and 6.3 mg for females over the entire study period. For the 12 patients with baseline body weight less than 40 kg, the weighted average daily dose was 0.06 to 0.11 mg/kg (0.8-4.3 mg) over the entire study period.

Efficacy Results

At baseline, 37 (77%) patients had HbA1c values of 7% or greater, 19 (40%) had HbA1c values of 9% or greater, 33 (69%) had fasting plasma glucose values of 126 mg/dL or greater, 17 (35%) had fasting triglyceride values of 500 mg/dL or greater, and 11 (23%) had fasting triglyceride values of 1000 mg/dL or greater.

Patients treated with MYALEPT had mean/median reductions in HbA1c, fasting glucose, and triglycerides at 1 year (Table 4). The changes in HbA1c, fasting glucose, and triglycerides observed at Month 4 were similar to those at 1 year. Concomitant antihyperglycemic and lipid-altering medication dosage regimens were not held constant during the study; for example, some patients treated with insulin had their dosage increased and others had large reductions or discontinuation of insulin.

Table 4: Results in an Open-Label, Single-Arm Study in Patients with Generalized Lipodystrophy Treated with MYALEPT (N=48)
Parameter | n | Baseline | Change from Baseline at Month 12
 |  | Mean (SD) | Mean (SD)
HbA1c (%) | 35 | 8.5 (2) | −2 (1.5)
Fasting Glucose (mg/dL) | 37 | 174 (85) | −49 (75)
 |  | Median (Q1, Q3) | Median Change (Q1, Q3)
Fasting Triglycerides (mg/dL) | 36 | 348 (176, 769) | −184 (−643, −21)
 |  |  | Median Percent Change (Q1, Q3)
 |  |  | −55 (−77, −20)%
SD = standard deviation; Q = quartile

Among 28 patients with generalized lipodystrophy who had a baseline HbA1c 7% or greater and data available at Month 12, the mean (SD) baseline HbA1c was 9.3 (1.5%) and the mean reduction in HbA1c at Month 12 was 2.4%.

Among 12 patients with generalized lipodystrophy who had a baseline triglyceride level 500 mg/dL or greater and data available at Month 12, the median baseline triglyceride level was 1527 mg/dL and the median reduction in triglycerides at Month 12 was 1117 mg/dL.

16 HOW SUPPLIED/STORAGE AND HANDLING

16.1 How Supplied

- MYALEPT (metreleptin) for injection for subcutaneous administration is supplied in a single carton containing one vial for reconstitution (NDC 10122-210-02).
- Each vial contains 11.3 mg metreleptin (as a sterile, white, solid, lyophilized cake) to deliver 5 mg per mL of metreleptin when reconstituted with 2.2 mL of BWFI or WFI.

16.2 Storage and Handling

- MYALEPT should be stored in the refrigerator at 36°F to 46°F (2°C to 8°C) and protected from light until preparing for use. Keep MYALEPT vials in the carton when not in use.
- MYALEPT should not be used past the expiration date.
- Do not freeze MYALEPT.
- Do not use if the white lyophilized cake is discolored.
- Use with BWFI: when MYALEPT is reconstituted with BWFI, the vial can be used for multiple doses within 3 days when stored in the refrigerator at 36°F to 46°F (2°C to 8°C) and protected from light.
- Use with WFI: when MYALEPT is reconstituted with WFI, the vial can be used for a single dose should be administered immediately. Unused reconstituted solution cannot be saved for later use and should be discarded.
- After reconstitution, the vials should not be frozen (below 0°C) or shaken vigorously. If the reconstituted product is inadvertently frozen, it should be thrown away.
- After reconstitution, the mixture should be clear and colorless. Do not use if visible particulates are present in the solution.
- Keep out of the reach of children.

17 PATIENT COUNSELING INFORMATION

See FDA-approved Patient Labeling (Medication Guide).

Risk of Neutralizing Antibodies

Advise patients that neutralizing antibodies may result in loss in activity of endogenous leptin or loss of efficacy of MYALEPT. Advise patients on symptoms or signs that would warrant antibody testing [see Warnings and Precautions (5.1) and Adverse Reactions (6.2)].

Risk of Lymphoma

Advise patients that lymphoma has been reported in patients both treated and not treated with MYALEPT. Advise patients on symptoms or signs that indicate changes in hematologic status and the importance of routine laboratory assessments and physician monitoring [see Warnings and Precautions (5.2)].

Risk of Hypoglycemia

Advise patients that the risk of hypoglycemia is increased when MYALEPT is used in combination with insulin or an insulin secretagogue (e.g., sulfonylurea). Explain the symptoms, treatment, and conditions that predispose to development of hypoglycemia to the patient. Advise patients who are taking concomitant insulin, especially those on high doses, or an insulin secretagogue, to closely monitor blood glucose. Hypoglycemia management should be reviewed and reinforced when initiating MYALEPT therapy, particularly when concomitantly administered with insulin or an insulin secretagogue [see Warnings and Precautions (5.4)].

Risk of Autoimmune Disease

Advise patients that worsening of autoimmune disease has been reported during the clinical study of MYALEPT. Advise patients with a history of autoimmune disease on symptoms or signs that indicate exacerbation of underlying autoimmune disease and the importance of routine laboratory assessments and physician monitoring [see Warnings and Precautions (5.5)].

Risk of Hypersensitivity Reactions

Inform patients that hypersensitivity reactions have been reported during use of MYALEPT. If symptoms of hypersensitivity reactions occur, patients should seek medical advice [see Warnings and Precautions (5.6)].

Instructions

- Inform patients that each vial of MYALEPT requires reconstitution with BWFI or preservative-free WFI, and administration as subcutaneous injection using a syringe and needle. Injections can be given at any time of the day, with or without meals.
- Patients and caregivers should receive proper training in how to prepare and administer the correct dose of MYALEPT prior to self-administration. The first dose of MYALEPT should be administered by the patient or caregiver under the supervision of a qualified healthcare professional.
- Advise patients on appropriate syringe for administration, dosing regimen, injection technique, and the importance of proper storage of MYALEPT. Care should be taken to avoid intramuscular injection, especially in patients with minimal subcutaneous adipose tissue.
- Advise patients to read the Instructions for Use for complete administration instructions. The MYALEPT Medication Guide and Instructions for Use should be reviewed before starting therapy and each time the prescription is refilled.
- When discontinuing MYALEPT in patients with a history of pancreatitis and/or severe hypertriglyceridemia, instruct patients to taper their dose over a one-week period. Advise patients that additional monitoring of triglyceride levels and possible initiation or dose adjustment of lipid-lowering medications may be considered [see Dosage and Administration (2.5)].

Manufactured by:

Chiesi Farmaceutici S.p.A.

Via Palermo 26/A, 43122 Parma, Italy

US License No.2245

Manufactured for:

Chiesi USA, Inc.,

Cary NC, 27518, USA.

Product of Austria.

Myalept is a registered trademark owned by the Chiesi Group.

©2024 Chiesi USA. All rights reserved.

7488-00 70016026-01

MEDICATION GUIDE

MYALEPT® (MAI-uh-lept)
(metreleptin)
for injection, for subcutaneous use

What is the most important information I should know about MYALEPT?
MYALEPT may cause serious side effects, including:

- risk for loss of endogenous leptin activity or loss of MYALEPT efficacy due to neutralizing antibodies.
  Some people who use MYALEPT make antibodies in their blood that may reduce how well the leptin in your body (endogenous) works or how well MYALEPT works. Side effects may include:
  - infection
  - problems with blood sugar, including diabetes
  - an increase in the amount of fat in your blood (triglycerides)
- lymphoma (a type of blood cancer). There may be an increased risk of getting lymphoma when you use MYALEPT.

MYALEPT is only available through a restricted program called the MYALEPT Risk Evaluation and Mitigation Strategy (REMS) Program. For more information about the MYALEPT REMS Program go to www.myaleptrems.com or call 1-855-669-2537.

What is MYALEPT?
MYALEPT is a prescription medicine used with a diet recommended by your healthcare provider to treat problems caused by not having enough leptin in your body (leptin deficiency) in people with congenital or acquired generalized lipodystrophy.

- It is not known if MYALEPT is safe and effective when used:
  - to treat problems (complications) caused by partial lipodystrophy
  - to treat liver disease, including non-alcoholic steatohepatitis (NASH)
- MYALEPT should not be used to treat:
  - people with HIV-related lipodystrophy
  - people with metabolic disease, including diabetes mellitus and hypertriglyceridemia, without signs or symptoms of congenital or acquired generalized lipodystrophy

Do not use MYALEPT if you:

- have general obesity that is not caused by a congenital leptin deficiency.
- are allergic to metreleptin or any of the ingredients in MYALEPT. See the end of this Medication Guide for a complete list of ingredients in MYALEPT.
  Talk to your healthcare provider right away if you have any symptoms of an allergic reaction including a rash or itching (hives).
  Symptoms of a severe allergic reaction may include:
  - swelling of your face, lips, tongue, or throat
  - problems breathing or swallowing
  - severe rash or itching
  - fainting or feeling dizzy
  - very rapid heartbeat

What should I tell my healthcare provider before using MYALEPT?
Before using MYALEPT, tell your healthcare provider if you:

- have or have had problems with your blood cells including low blood cell counts, especially white blood cells
- have or have had problems with your bone marrow
- have or have had swollen lymph nodes (lymphadenopathy)
- have or have had lymphoma
- use insulin or a sulfonylurea
- have or have had problems with your immune system (autoimmune disease)
- have or have had problems with your pancreas (pancreatitis)
- have high blood triglyceride levels
- have any other medical conditions
- are pregnant or plan to become pregnant. It is not known if MYALEPT will harm your unborn baby
  - If you become pregnant while using MYALEPT, talk to your healthcare provider about registering with a program to collect information about the outcomes of moms and babies exposed to MYALEPT during pregnancy. You can enroll in the MYALEPT program by calling 1-855-669-2537.
- are breastfeeding or plan to breastfeed. It is not known if MYALEPT passes into your breastmilk. Talk to your healthcare provider about the best way to feed your baby while taking MYALEPT.

Tell your healthcare provider about all the medicines you take, including prescription and over-the-counter medicines, vitamins, and herbal supplements.
Know the medicines you take. Keep a list of them with you to show your healthcare provider and pharmacist when you get a new medicine.

How should I use MYALEPT?

- See the Instructions for Use that come with MYALEPT for detailed instructions on using MYALEPT the right way.
- Use MYALEPT exactly as your healthcare provider tells you to.
- Your healthcare provider will tell you how much MYALEPT to use and when to use it. Do not change your dose unless your healthcare provider tells you to.
  - Do not suddenly stop using MYALEPT. Stopping MYALEPT suddenly may cause a serious problem with your pancreas (pancreatitis) and very high triglycerides.
  - If your healthcare provider decides that you should stop using MYALEPT, your healthcare provider should slowly decrease your dose (taper) over 1 week.
- MYALEPT is injected 1 time a day at the same time each day.
- MYALEPT can be used with or without food.
- If you miss a dose of MYALEPT, take it as soon as you remember. Take your regular dose the next day at your normal time. Do not take more than your regular daily dose in a single day. Do not take an extra dose or increase the amount of your dose to make up for a missed dose.
- Do not mix MYALEPT and insulin in the same syringe or vial. Although MYALEPT and insulin doses may be given at the same time, do not inject MYALEPT and insulin in the same injection site.
- When MYALEPT is used in newborns or infants, your healthcare provider will tell you if MYALEPT should be mixed with a liquid called sterile water for injection (WFI) (preservative-free). For older children and adults, bacteriostatic water for injection (BWFI) may be used.
- MYALEPT is given as an injection under the skin (subcutaneous) of your stomach (abdomen), thigh, or upper arm. Do not inject MYALEPT into a vein or muscle.

What are the possible side effects of MYALEPT?
MYALEPT may cause serious side effects, including:

- See "What is the most important information I should know about MYALEPT?"
- low blood sugar (hypoglycemia). You may get low blood sugar if you use MYALEPT with another medicine that can cause low blood sugar, such as insulin or sulfonylurea. The dose of your insulin or sulfonylurea may need to be lowered while you use MYALEPT. Signs and symptoms of low blood sugar may include:

- shakiness
- weakness
- hunger

- sweating
- dizziness
- fast heart beat

- headache
- confusion
- feeling jittery

- drowsiness
- irritability

Talk with your healthcare provider about how to recognize and treat low blood sugar. Make sure that your family and other people around you a lot know how to recognize and treat low blood sugar.

- autoimmunity. People who have or have had certain problems with their immune system (autoimmune disease) may have worsening of their symptoms with MYALEPT. Talk to your healthcare provider about what symptoms you should watch for that would warrant further testing.
- allergic reactions (hypersensitivity). Allergic reactions can happen in people who use MYALEPT. Talk to your healthcare provider right away if you have any symptom of an allergic reaction. See "
- benzyl alcohol toxicity. Serious side effects including death have happened in newborns or infants who have received the preservative benzyl alcohol. MYALEPT, when mixed with a liquid called bacteriostatic water for injection (BWFI), contains benzyl alcohol. MYALEPT, when mixed with a liquid called sterile water for injection (WFI) (preservative-free), contains no benzyl alcohol. When MYALEPT is used in newborns or infants, MYALEPT should be mixed with sterile water for injection (WFI).

The most common side effects of MYALEPT include:

- headache
- low blood sugar (hypoglycemia)
- decreased weight
- abdominal pain

Talk to your healthcare provider about any side effect that bothers you or that does not go away.
These are not all the side effects with MYALEPT. For more information, ask your healthcare provider or pharmacist.
Call your doctor for medical advice about side effects. You may report side effects to FDA at 1-800-FDA-1088.

How should I store MYALEPT?

- Store MYALEPT in the refrigerator between 36°F to 46°F (2°C to 8°C).
- KEEP MYALEPT vials in their carton and out of the light.
- Do not freeze MYALEPT.
- Do not use MYALEPT past the expiration date printed on the vial.
- Do not use MYALEPT if the white powder in the vial is discolored.
- After mixing, the MYALEPT liquid in the vial should be clear and colorless. Do not use MYALEPT if it is colored or cloudy, or has any lumps or particles in it. Throw the vial away and get a new one.
- After mixing, do not freeze or shake MYALEPT.
- MYALEPT mixed with BWFI:
  - MYALEPT can be used for more than 1 dose for up to 3 days when stored in the refrigerator between 36°F to 46°F (2°C to 8°C) and out of the light. Throw away any unused MYALEPT after 3 days.
- MYALEPT mixed with WFI:
  - Should be used right away. Throw away any unused MYALEPT, it cannot be saved for later use.

Keep MYALEPT and all medicines out of the reach of children.

General information about the safe and effective use of MYALEPT
Medicines are sometimes prescribed for purposes other than those listed in a Medication Guide. Do not use MYALEPT for a condition for which it was not prescribed. Do not give MYALEPT to other people, even if they have the same symptoms you have. It may harm them.
This Medication Guide summarizes the most important information about MYALEPT. If you would like more information, talk with your healthcare provider. You can ask your healthcare provider or pharmacist for information about MYALEPT that is written for health professionals.
For more information about MYALEPT, go to www.myalept.com or call MYALEPT Customer Service at 1-855-669-2537.

What are the ingredients in MYALEPT?
Active Ingredient: metreleptin
Inactive Ingredients: glutamic acid, glycine, sucrose, and polysorbate 20
MYALEPT is a registered trademark owned by the Chiesi Group. ©2024 Chiesi USA. All rights reserved.
Manufactured by:
Chiesi Farmaceutici S.p.A.
Parma, Italy
US License No.2245

Manufactured for:
Chiesi USA, Inc.,
Cary NC, 27518, USA.
Product of Austria.
7489-00 70015684-01

This Medication Guide has been approved by the U.S. Food and Drug Administration.

Revised 03/2024

Instructions for Use
MYALEPT® (MAI-uh-lept)
(metreleptin) for injection, for subcutaneous use
Vial

- A healthcare provider should show you how to inject MYALEPT before you use it for the first time. A healthcare provider should also watch you inject your MYALEPT dose the first time you inject it.
- Do not inject MYALEPT until your healthcare provider has shown you the right way to inject it. If you have questions or do not understand the instructions, talk to your healthcare provider or pharmacist.
- MYALEPT is only for use under the skin (subcutaneous).
- Do not share your MYALEPT needles with another person. You may give an infection to them, or get an infection from them.

This Instructions for Use is divided into 6 steps:

Step 1: Getting started

Step 2: Filling the 3 mL syringe with 2.2 mL of liquid

Step 3: Preparing MYALEPT

Step 4: Filling the syringe used for injecting MYALEPT

Step 5: Injecting MYALEPT

Step 6: Disposing of used needles and syringes

If at any time during these steps you have questions:

- See the "Common Questions" tab
- Call 1-855-669-2537
- Visit www.MYALEPT.com

Supplies you will need to give your MYALEPT (see Figure A).

Make sure you have all the supplies listed below BEFORE using MYALEPT.

You can get these supplies with a prescription from your healthcare provider, from a retail or hospital pharmacy, or the specialty pharmacy that distributes MYALEPT.

- a vial with liquid for mixing MYALEPT
  - Sterile water for injection should be used in newborns and infants
  - Bacteriostatic water for injection should be used for older children and adults
- a 3 mL syringe with a longer needle for mixing MYALEPT
- a vial with MYALEPT powder
- a 1 mL syringe (or smaller) with a shorter needle for injecting MYALEPT
- 2 alcohol wipes
- 1 sharps container for throwing away used needles and syringes. See "Disposing of used needles and syringes" at the end of these instructions.
- Stickers to note discard date for mixed medicine

How to read your syringes:

The 3 mL syringe has a longer needle (see Figure B).

The 3 mL syringe is the syringe you will use to mix MYALEPT. Always fill the 3 mL syringe with 2.2 mL of liquid. Do not inject yourself with the 3 mL syringe.

Figure B

The injection syringes have a shorter needle (see Figure C).

- People who weigh more than 88 pounds (lbs) (40 kg) should use a 1 mL syringe to administer their injection of MYALEPT. People who weigh 88 lbs (40 kg) or less should use either a 1 mL or smaller syringe because smaller amounts of MYALEPT are needed for injection. Using the wrong size syringe can cause you to measure the wrong amount of MYALEPT.

The 1 mL (or smaller) syringe is the syringe you will use to inject MYALEPT. Only use the 1 mL (or smaller) syringe to inject your dose of MYALEPT.

Step 1: Getting Started

Your dose of MYALEPT may change over time, depending on how MYALEPT works for you. So it is important to keep track of your dose. On the line below, write down your dose in mL and the date. Be sure to keep this up-to-date if your dose changes:

- Take 1 MYALEPT vial out of the refrigerator 10 minutes before you plan to inject to allow it to reach room temperature.
- Set 1 vial with the liquid you will need to mix MYALEPT on your work surface.
- Check the powder in the MYALEPT vial. It should be white. Do not use MYALEPT if the powder is discolored. Throw it away and get a new one.
- Check the expiration date printed on the MYALEPT vial. Do not use MYALEPT past the expiration date printed on the vial (see Figure D).

Figure D

For this step, you will need:

Vial with liquid for mixing
a dose of MYALEPT

Vial with powder
(MYALEPT)

Alcohol wipes

Wash your hands with soap and water. | Remove 2 alcohol wipes from their wrappers. Place the wipes on their wrappers to keep them clean. | Use your thumb to remove the caps from the vials. | Clean the tops of the vials with one of the alcohol wipes.

STEP 2: Filling the 3 mL syringe (used to mix MYALEPT) with 2.2 mL of liquid

For this step, you will need:

A 3 mL syringe (with longer needle) used to mix MYALEPT

Vial with liquid
(from Step 1)

Sharps disposal container

Take the 3 mL syringe out of the plastic wrapper. Always use a new syringe.

Pull the needle cover straight off. Do not twist the needle when removing the cover.; Put the needle cover in the sharps disposal container. | Pull down the plunger to fill the syringe with air.; You must first fill the syringe with air and put that air into the vial to make it easier to later fill the syringe with liquid. | Line up the top rim of the plunger with the black 2.2 mL line.

Set the vial with the liquid on the work surface. Insert the needle into the top of the vial. | Push the plunger down all the way to fill the vial with air.

With the needle still in the vial, turn the vial and syringe upside down.; Keep the whole needle in the liquid. | Pull down the plunger until the top rim of the plunger lines up with the black 2.2 mL line. | Check to see if there is an air pocket in the syringe.; If you see an air pocket, tap the side of the syringe to move the air pocket to the top of the syringe. | Push the plunger up to remove the air pocket.; You must remove the air pocket to be able to fill the syringe with 2.2 mL of liquid.

Tip: You will always fill the 3 mL syringe with 2.2 mL of liquid.

Check to see if there are large air bubbles in the syringe.; If you see large air bubbles in the syringe, tap the syringe to move the air bubbles to the top.; If there are a few small bubbles left, that is okay. | Push the plunger up to remove as many large air bubbles as you can. | Pull down the plunger so the top rim of the plunger lines up with the black 2.2 mL line. Keep the whole needle in the liquid. | Remove the needle from the vial. Be careful not to move the plunger.; Keep the syringe in your hand. Do not set it down.; For instructions on how to discard the used vial of liquid, read the carton that contained those vials.

STEP 3: Preparing MYALEPT

Note: If you already mixed your MYALEPT before today, go to "Using a vial of mixed MYALEPT" at the end of this step.

Option 1: Mixing a new vial of MYALEPT:

For this step, you will need:

The 3 mL syringe filled with 2.2 mL of liquid (from Step 2)

Vial with powder (from Step 1)

Sharps disposal container

Set the vial with the MYALEPT powder on the work surface. Insert the needle straight down into the center of the vial. | Then tilt the vial so that the tip of the needle is pointing toward the inside wall of the vial. | With your thumb, slowly push the plunger down all the way.; The liquid should go down the inside wall of the vial. | Make sure you add the liquid slowly so that bubbles do not form in the vial.; No liquid should be left in the syringe.

While keeping the plunger all the way down, take the needle out of the vial.; Throw away the syringe with the needle still attached into your sharps disposal container.; Do not recap the needle. Recapping the needle can lead to a needlestick injury. | To mix the powder and liquid, move the vial gently in a circle (swirl) until the liquid is clear. Do not shake the vial. | When the medicine is mixed well, the liquid should be clear. You should not see any clumps, powder, bubbles, or foam.

Tip: If your vial of MYALEPT is not mixed well, go back to Step 3c.

Note: Go to Step 4 if you just mixed a new vial of MYALEPT.

Option 2: Using a vial of mixed MYALEPT:

Note: For newborns or infants using MYALEPT, throw away any unused mixed MYALEPT right away. Do not store it for reuse.

For this step, you will need:

Vial of mixed MYALEPT

Alcohol wipes

Choose a clean, flat work surface large enough to let you prepare the medicine.

Take 1 vial of mixed MYALEPT out of the refrigerator. Only MYALEPT mixed with bacteriostatic water for injection can be stored for reuse. You must use the vial within 2 days after the day the medicine was mixed. | Set the vial of mixed MYALEPT on the work surface for 10 to 15 minutes so that it comes to room temperature. | Wash your hands with soap and water. | Remove 2 alcohol wipes from their wrappers. Place the wipes on their wrappers to keep them clean.

Clean the top of the vial with the alcohol wipe. | Check that the MYALEPT is mixed well and is clear. You should not see any clumps, powder, bubbles, or foam. If you see clumps, powder, bubbles, or foam, throw away the vial in the sharps disposal container.

Important: Do not mix any liquid or mixed medicine from another vial with the vial you just cleaned.

STEP 4: Filling the syringe used for injecting MYALEPT

Patients greater than 40 kg should use a 1 mL syringe for administration. In pediatric patients, small volumes for administration can result in medication errors when measured incorrectly. Smaller syringe sizes may be more appropriate for pediatric patients weighing less than or equal to 25 kg. Ensure the proper size syringe is selected.

The table below shows how a dose of MYALEPT (mg) is converted to solution volume (mL) and the injection syringe marks (units) that correspond with the dose.

Conversion of MYALEPT Dose to Unit Measurement for Injection
DOSE OF MYALEPT | AMOUNT OF MIXED MYALEPT SOLUTION TO INJECT (TUBERCULIN SYRINGE USERS) | AMOUNT OF MIXED MYALEPT SOLUTION TO INJECT (INSULIN SYRINGE USERS)
0.30 mg | 0.06 mL | 6 units
0.36 mg | 0.07 mL | 7 units
0.42 mg | 0.08 mL | 8 units
0.48 mg | 0.09 mL | 9 units
0.54 mg | 0.10 mL | 10 units
0.60 mg | 0.12 mL | 12 units
0.66 mg | 0.13 mL | 13 units
0.72 mg | 0.14 mL | 14 units
0.78 mg | 0.15 mL | 15 units
0.84 mg | 0.16 mL | 16 units
0.90 mg | 0.18 mL | 18 units
0.96 mg | 0.19 mL | 19 units
1.02 mg | 0.20 mL | 20 units
1.08 mg | 0.21 mL | 21 units
1.14 mg | 0.22 mL | 22 units
1.20 mg | 0.24 mL | 24 units
1.26 mg | 0.25 mL | 25 units
1.32 mg | 0.26 mL | 26 units
1.38 mg | 0.27 mL | 27 units
1.44 mg | 0.28 mL | 28 units
1.50 mg | 0.30 mL | 30 units
1.56 mg | 0.31mL | 31 units
1.62 mg | 0.32 mL | 32 units
1.68 mg | 0.33 mL | 33 units
1.74 mg | 0.34 mL | 34 units
1.80 mg | 0.36 mL | 36 units
1.86 mg | 0.37 mL | 37 units
1.92 mg | 0.38 mL | 38 units
1.98 mg | 0.39 mL | 39 units
2.04 mg | 0.40 mL | 40 units
2.10 mg | 0.42 mL | 42 units
2.16 mg | 0.43 mL | 43 units
2.22 mg | 0.44 mL | 44 units
2.28 mg | 0.45 mL | 45 units
2.34 mg | 0.46 mL | 46 units
2.40 mg | 0.48 mL | 48 units
2.5 mg | 0.50 mL | 50 units
3.75 mg | 0.75 mL | 75 units
5.00 mg | 1.00 mL | 100 units
6.25 mg | 1.25 mL | 125 units
7.50 mg | 1.5 mL | 150 units
8.75 mg | 1.75 mL | 175 units
10.00 mg | 2.00 mL | 200 units

For this step, you will need:

A (1 mL or smaller) syringe (with shorter needle) used to inject MYALEPT
Examples:

Vial of mixed MYALEPT (from Step 3)

Sharps disposal container

Remove the injection syringe from the plastic wrapper. Always use a new syringe.

Firmly grip the needle base.

Pull the needle cover straight off.

Throw away the needle cover in the sharps disposal container.

Pull down the plunger until the top rim of the plunger lines up with the black line of the dose prescribed by your healthcare provider.

You must first fill the syringe with air and put that air into the vial to make it easier to later fill the syringe with liquid.

Hold the vial with the mixed MYALEPT. Insert the needle into the top of the MYALEPT vial. | Push the plunger down all the way, to fill the vial with air.

With the needle still in the vial, turn the vial and syringe upside down.; Keep the whole needle in the liquid. It is okay if the plunger moves down. | Pull down the plunger until the top rim of the plunger lines up with the black line of the dose prescribed by your healthcare provider. | Check to see if there is an air pocket in the syringe.; If you see an air pocket, tap the side of the syringe to move the air pocket to the top of the syringe. | Push the plunger up to remove the air pocket.; You must remove the air pocket to be able to fill the syringe with a full dose of MYALEPT.

Tip: If your prescribed dose is more than 1 mL, you will need to use 2 separate injections to take your full daily dose. Repeat Step 4 to fill the second syringe.

Check to see if there are large air bubbles in the syringe.; If you see large air bubbles in the syringe, tap the side of the syringe to move the air bubbles to the top. If there are a few small bubbles left, that is okay. | Push the plunger up to remove as many large air bubbles as you can. | Pull down the plunger again until the top rim of the plunger lines up with the black line of the dose prescribed by your healthcare provider. | Remove the needle from the vial.; Set the vial down. Do not set the syringe down.

STEP 5: Injecting MYALEPT

For this step, you will need:

Syringe filled with your
MYALEPT dose
(from Step 4)

Alcohol wipe
(from Step 1)

Sharps disposal
container for used syringes and needles

Choose an injection site that you will use to inject your MYALEPT.

The recommended injection sites are an area of your body that has the most fat, such as the stomach (abdomen), thigh, or the back of your upper arm.
You can use the same area of the body for each injection. But be sure to choose a different injection site in that area.

If you inject other medicines you should choose a different site from where you inject MYALEPT. Do not inject MYALEPT in the same site as your other medicines.

Use an alcohol wipe to clean the injection site.

Let the alcohol dry before you move on to 5c.

Pinch the skin with one hand.

With the other hand, hold the syringe like a pencil.
Insert the needle into the skin at an angle.
Do not insert the needle straight up and down.

Let go of the skin.
Use your thumb to push the plunger down until it stops.

Take the needle out of your skin.

Important:

Inject MYALEPT under the skin (subcutaneous). Do not inject MYALEPT into a muscle or vein.

Throw away the used syringe with the needle still attached in your sharps disposal container. See "Disposing of used needles and syringes" at the end of this IFU.
Do not recap the needle. Recapping the needle can lead to a needlestick injury.

Important:

Unused MYALEPT mixed with sterile water for injection (newborns or infants), must be thrown away.

Do not store it for reuse.

MYALEPT mixed with bacteriostatic water for injection can be stored for reuse.

Store the vial of mixed MYALEPT in the refrigerator as soon as you are done. | Looking at a calendar, count 2 days after the day you mixed the MYALEPT.; For example, if you mixed MYALEPT on Monday, January 2, you would throw it away after your dose on Wednesday, January 4. | Write that date on the stickers found to the right. | Place the sticker on the vial of mixed MYALEPT.

Important:

Stickers to Note the Last Day You Can Use MYALEPT When Mixed with Bacteriostatic Water for Injection

STEP 6: Disposing of used needles and syringes:

- Put your used needles and syringes in an FDA-cleared sharps disposal container right away after use. Do not throw away (dispose of) loose needles and syringes in your household trash.
- If you do not have an FDA-cleared sharps disposal container, you may use a household container that is:
  - made of heavy-duty plastic
  - can be closed with a tight-fitting, puncture-resistant lid, without sharps being able to come out
  - upright and stable during use
  - leak-resistant, and
  - properly labeled to warn of hazardous waste inside the container
- When your sharps disposal container is almost full, you will need to follow your community guidelines for the right way to dispose of your sharps disposal container. There may be state or local laws about how you should throw away used needles and syringes. For more information about safe sharps disposal, and for specific information about sharps disposal in the state you live in, go to the FDA's website at: http://www.fda.gov/safesharpsdisposal.

Common questions

Questions about storing and traveling with MYALEPT | page 15
Questions about preparing and mixing your dose of MYALEPT | pages 15-16
Questions about injecting MYALEPT | page 16
Questions about MYALEPT supplies | page 16

Common questions

Questions about storing and traveling with MYALEPT

1Q | How do I store a vial of powder (MYALEPT) and mixed MYALEPT?
A | The vial of powder has a white cap. The vial of mixed medicine is the vial to which you applied the sticker.; - These vials should be kept in their carton in the refrigerator until you are ready to use them - Store these vials in their carton so they can be protected from light - Do not freeze or heat these vials
2Q | How long can I leave a vial of powder or mixed MYALEPT at room temperature?
A | A vial of powder or MYALEPT mixed with bacteriostatic water for injection can be left at room temperature for up to 4 hours. MYALEPT mixed with sterile water for injection should be used right away. Throw away any unused mixed MYALEPT. If you are unsure about whether you can use a vial of powder or mixed MYALEPT, call 1-855-6MYALEPT.
3Q | What do I do with a vial of powder or mixed MYALEPT if it has been frozen or heated?
A | If a vial of powder or mixed MYALEPT has been frozen or heated, throw it away in the sharps disposal container.
4Q | What do I do with a vial of mixed MYALEPT if there is not a full dose left?
A | Ask your healthcare provider how to use or store a vial of mixed MYALEPT that contains less than a full dose.
5Q | How do I take MYALEPT if I am away from home or traveling?
A | To take a dose of MYALEPT if you are away from home or traveling, you must take all of your supplies with you. Do not fill a syringe or prepare a dose ahead of time and take it with you.

Questions about preparing and mixing your dose of MYALEPT

6Q | What should I do if I touch the top of a vial after I have cleaned it?
A | Clean the top of the vial again with a new alcohol wipe.
7Q | What should I do if my dose is written in mg (milligrams), not mL (milliliters)?
A | If your dose of MYALEPT is written in mg and not mL, call your pharmacist. Your pharmacist can give you your dose in mL. Do not try to prepare a dose of MYALEPT if your dose is in mg.
8Q | What should I do if there are air bubbles or air pockets in the syringe?
A | Follow steps 2g (page 5) and 2h (page 6) to remove air bubbles or an air pocket from the syringe when filling it with liquid. Follow steps 4g and 4h (page 11) to remove air bubbles or an air pocket from the syringe when filling it with MYALEPT. Check to see if there are large air bubbles in the syringe. If so, tap the syringe to move the air bubbles to the top. If there are still a few small air bubbles left in the syringe after these steps, that is okay. The air bubbles will not harm you.
9Q | What if the needle comes off the syringe used to mix MYALEPT when I am trying to remove the needle cover?
A | With the needle cover still on the needle, twist the needle back onto the syringe. Firmly grip the syringe and pull the needle cover straight off. Do not twist the syringe or needle when pulling off the needle cover.
10Q | What if the needle comes off the syringe used to inject MYALEPT when I am trying to remove the needle cover?
A | With the needle cover still on the needle, firmly push the needle back onto the syringe. Grip the base of the needle as firmly as you can between your index finger and thumb while pulling on the needle cover.
11Q | What do I do if I see foam in a vial of medicine I am mixing?
A | If foam forms in the vial of medicine as you swirl it, let the vial sit on the work surface until the foam is gone.
12Q | Can I fill a syringe with a dose of mixed MYALEPT and save it to use later?
A | A dose of MYALEPT should be taken right after it is mixed. Do not fill a syringe or prepare a dose for later use.

Questions about injecting MYALEPT

13Q | What are some tips for injecting MYALEPT?
A | Try these tips to help you prepare for your injection with MYALEPT:; - Know the steps in the process. To get to know the steps, read this booklet ahead of time. It may help to read the steps out loud. If you have questions about how to inject, make sure to ask your healthcare provider - Find a place that is clean and well lit in which you can do the injection - Ask for help. You may feel more comfortable if a care partner does the injection for you - Put ice on the injection site. You may want to use ice at the injection site, after your injection, to help lessen some of the pain you might feel - Make sure the vial with powder (MYALEPT) is at room temperature before you mix and inject it. To do this, take a vial with powder out of the refrigerator and set it out for 10 to 15 minutes

Questions about MYALEPT supplies

14Q | How do I obtain the supplies needed to inject MYALEPT?
A | The standard supplies needed to inject MYALEPT include needles, syringes, liquid for mixing and a disposal container. Your healthcare provider will give you a prescription for these supplies which can be filled by a retail or hospital pharmacy, or the specialty pharmacy who distributes MYALEPT.
15Q | How do I store the other supplies that are needed to prepare and inject a dose of MYALEPT?
A | Store syringes, vials of liquid with colored caps, alcohol wipes, and sharps disposal container at room temperature or at the temperature that is written on the package they came in. Be sure to check the expiration date on the packages of your supplies before use. Do not use expired supplies.

To learn more about MYALEPT

- Talk with your healthcare provider
- Read the Medication Guide that came with MYALEPT. The Medication Guide can help answer your questions about MYALEPT, such as what it is used for, possible side effects, and when to take it
- Visit www.MYALEPT.com or call 1-855-6MYALEPT for FREE ongoing support and services

This Instructions for Use has been approved by the U.S. Food and Drug Administration.

MYALEPT is a registered trademark owned by the Chiesi Group. ©2024 Chiesi USA. All rights reserved.

Manufactured by:

Chiesi Farmaceutici S.p.A.
Parma, Italy
US License No. 2245

Manufactured for:
Chiesi USA, Inc.,
Cary NC, 27518, USA.
Product of Austria.

7487-00

Issued March 2024

PRINCIPAL DISPLAY PANEL - 11.3 mg Vial Label

myalept®
(metreleptin) For Injection
11.3 mg per vial
Subcutaneous use only.

NDC10122-210-01
Rx Only
Sterile

Single-dose vial if reconstituted with Water for Injection.

Multi-dose vial if reconstituted with Bacteriostatic
Water for Injection.

Store refrigerated: 36°F to 46°F (2°C to 8°C).
Manufactured by:Chiesi Farmaceutici S.p.A., Parma, Italy
US License No.2245

PRINCIPAL DISPLAY PANEL - 11.3 mg Vial Carton

Rx Only
NDC 10122-210-02

myalept®
(metreleptin) For Injection
11.3 mg per vial

SUBCUTANEOUS USE ONLY

Dispense the enclosed Medication Guide to each patient.

Single-dose vial if reconstituted with Water for Injection.
Discard after each use.

Multi-dose vial if reconstituted with Bacteriostatic Water
for Injection. Must be used within 3 days after
reconstitution when refrigerated.